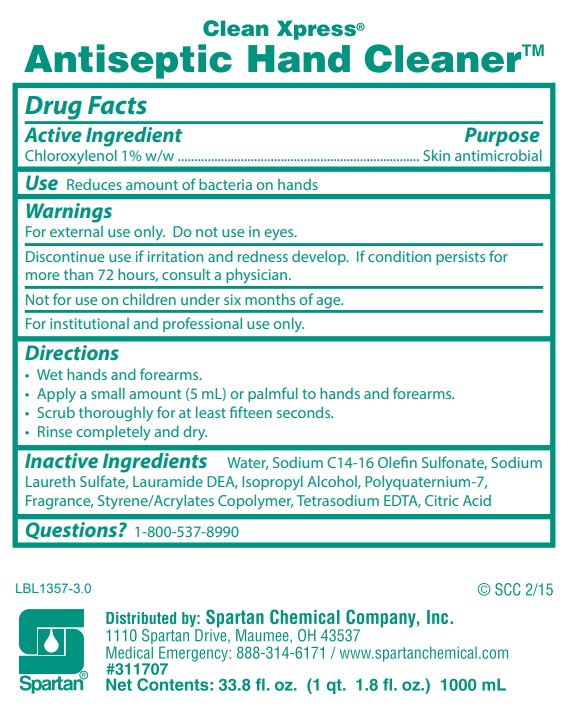 DRUG LABEL: Clean Xpress Antiseptic Hand Cleaner
NDC: 64009-338 | Form: SOAP
Manufacturer: Spartan Chemical Company, Inc.
Category: otc | Type: HUMAN OTC DRUG LABEL
Date: 20251006

ACTIVE INGREDIENTS: CHLOROXYLENOL 10 mg/1 mL
INACTIVE INGREDIENTS: WATER; SODIUM C14-16 OLEFIN SULFONATE; SODIUM LAURETH SULFATE; LAURIC DIETHANOLAMIDE; ISOPROPYL ALCOHOL; POLYQUATERNIUM-7 (70/30 ACRYLAMIDE/DADMAC; 1600000 MW); EDETATE SODIUM; CITRIC ACID MONOHYDRATE

Active Ingredient

Chloroxylenol 1% w/w

Purpose

Skin antimicrobial

Use

Reduces amount of bacteria on hands.

Warnings

- For external use only. Do not use in eyes.
- Discontinue use if irritation and redness develop. If condition persists for more than 72 hours consult a doctor.
- Not for use on children under six months of age.
- For institutional and professional use only.

Directions

- Wet hands and forearms.
- Apply a small amount (5 mL) or palmful to hands and forearms.
- Scrub thoroughly for at least 15 seconds.
- Rinse completely and dry.

Inactive Ingredients

Water, Sodium C14-16 Olefin Sulfonate, Sodium Laureth Sulfate, Lauramide DEA, Isopropyl Alcohol, Polyquaternium-7, Fragrance, Styrene/Acrylates Copolymer, Tetrasodium EDTA, Citric Acid

Questions?

1-800-537-8990